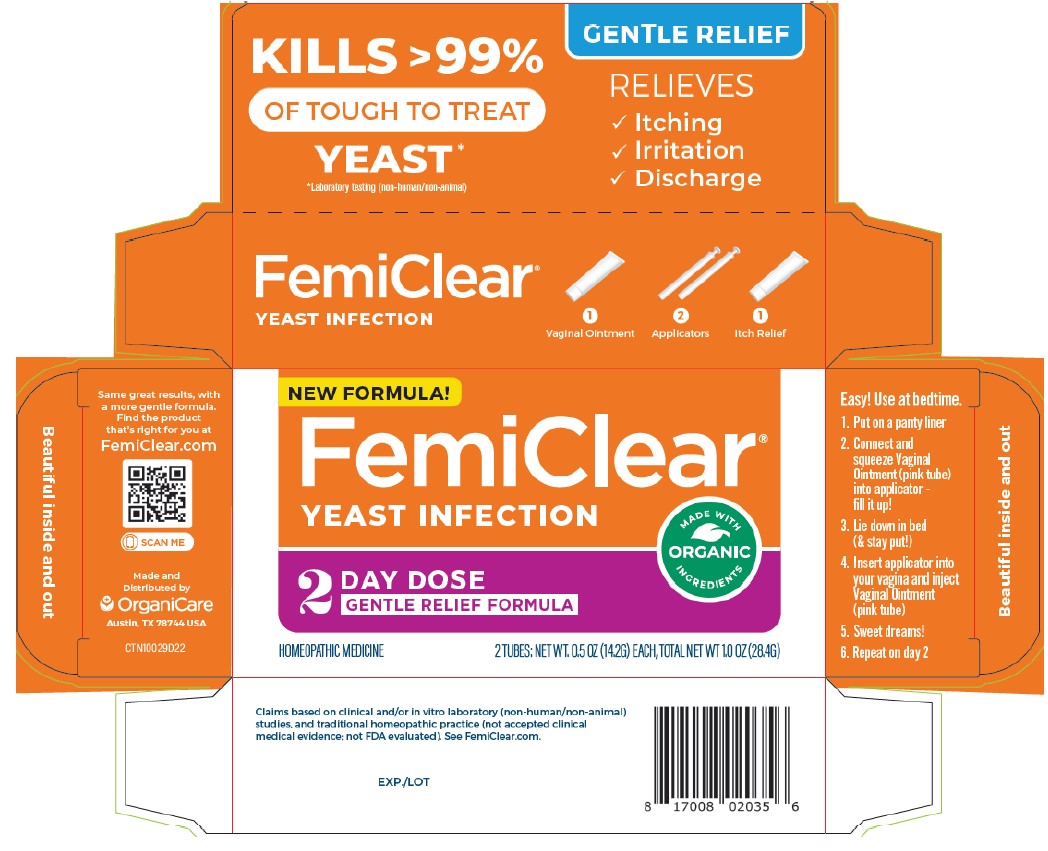 DRUG LABEL: FemiClear 2 Day Gentle
NDC: 71042-029 | Form: OINTMENT
Manufacturer: OrganiCare Nature's Science, LLC
Category: homeopathic | Type: HUMAN OTC DRUG LABEL
Date: 20241212

ACTIVE INGREDIENTS: CALENDULA OFFICINALIS WHOLE 0.01 g/100 g; MELALEUCA CAJUPUTI WHOLE 0.01 g/100 g
INACTIVE INGREDIENTS: OLIVE OIL 88 g/100 g

FemiClear 2 Day Gentle

Active Ingredients

Vaginal Ointment
Calendula 6X HPUS ............................................................................................... Healing agent
Melaleuca 6X HPUS........................................................................................... Anti-yeast agent
Olive Extract (Oleuropein) 3X HPUS ............................................Anti-microbial and healing agent
Itch Relief
Chamomilla 3X HPUS ............................................................... Anti-itch and inflammatory agent
Olive Extract (Oleuropein) 3X HPUS ............................................Anti-microbial and healing agent

Warnings

For vaginal use only.
Do not use if you have never had a vaginal yeast infection diagnosed by a doctor.
FemiClear may damage condoms and diaphragms and cause them to fail.

Ask a doctor before use if you have:

 vaginal itching and discomfort for the first time
 lower abdominal, back or shoulder pain, fever, chills, nausea, vomiting or
foul-smelling vaginal discharge. You may have a more serious condition.
 vaginal yeast infections often (such as once a month or 3 in 6 months). You could be
pregnant or have a serious underlying medical cause for your symptoms, including
diabetes or a weakened immune system.
 been exposed to the human immunodeficiency virus (HIV) that causes AIDS

Do not use

 if you are allergic to any ingredient in this product

When using this product

 do not use tampons, douches, spermicides or other vaginal products. Condoms and
diaphragms may be damaged and fail to prevent pregnancy or sexually transmitted
infections (STIs)
 do not have vaginal intercourse
 mild increase in vaginal burning, itching, or irritation may occur
 if you do not get complete relief, ask a doctor before using another product

Warnings (Cont.)

Stop use and ask a doctor if
 symptoms do not get better in 3 days
 symptoms last more than 7 days
 you get a rash or hives, abdominal pain, fever, chills, nausea, vomiting or
foul-smelling discharge

If pregnant or breast-feeding, ask a healthcare professional before use.

Keep out of the reach of children. If swallowed, get medical help or contact
a Poison Control Center right away.

Directions

 Adults and children 12 years or over:
Vaginal Ointment (pink tube): use at bed time, read enclosed instructions for
complete directions.
 to protect clothes, use panty liner.
 fill applicator with Vaginal Ointment (pink tube) - use 1/2 of the pink tube
 lie down in bed. Insert applicator into vagina and inject FemiClear. Remain lying
down to avoid leakage.
 discard applicator after use. DO NOT reuse.
 repeat on second night - use other 1/2 of the pink tube
Itch Relief: squeeze ointment onto fingertips. Apply onto itchy, irritated skin
outside the vagina (vulva) as needed.
 Children under 12 years: ask a doctor

Other information

 do not use if applicator wrapper is torn, open or incompletely sealed
 do not use if seal over tube opening has been punctured
 do not purchase if carton is open
 Store at 68° – 77° F (20° C – 25° C) If liquefied, refrigerate 10 minutes to thicken.
 this a 2-dose treatment. Most women do not get complete relief of their symptoms in
just 2 days. Most women get some improvement in 2 days and complete relief by 7 days.

Inactive ingredients

Vaginal Ointment: beeswax, essential oil (natural fragrance), oxygenated olive oil
Itch Relief: beeswax, colloidal oatmeal, essential oil (natural fragrance),
oxygenated olive oil

Questions

Call 512.401.3572 or visit femiclear.com. OrganiCare, LLC, Austin, TX 78744, USA

Uses

-treats vaginal infections

-releaves external itching and irritation due to vaginal yeast inrfection

PURPOSE

-relieves external itching and irritation due to vaginal yeast inrfection

Directions

 Adults and children 12 years or over:
Vaginal Ointment (pink tube): use at bed time, read enclosed instructions for
complete directions.
 to protect clothes, use panty liner.
 fill applicator with Vaginal Ointment (pink tube) - use 1/2 of the pink tube
 lie down in bed. Insert applicator into vagina and inject FemiClear. Remain lying
down to avoid leakage.
 discard applicator after use. DO NOT reuse.
 repeat on second night - use other 1/2 of the pink tube
Itch Relief: squeeze ointment onto fingertips. Apply onto itchy, irritated skin
outside the vagina (vulva) as needed.
 Children under 12 years: ask a doctor